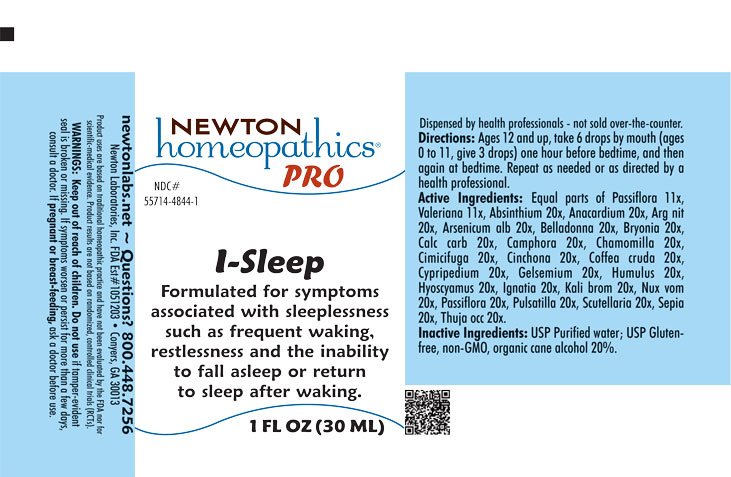 DRUG LABEL: I-Sleep
NDC: 55714-4844 | Form: LIQUID
Manufacturer: Newton Laboratories, Inc.
Category: homeopathic | Type: HUMAN OTC DRUG LABEL
Date: 20250918

ACTIVE INGREDIENTS: WORMWOOD 20 [hp_X]/1 mL; SEMECARPUS ANACARDIUM JUICE 20 [hp_X]/1 mL; SILVER NITRATE 20 [hp_X]/1 mL; ARSENIC TRIOXIDE 20 [hp_X]/1 mL; ATROPA BELLADONNA 20 [hp_X]/1 mL; BRYONIA ALBA ROOT 20 [hp_X]/1 mL; OYSTER SHELL CALCIUM CARBONATE, CRUDE 20 [hp_X]/1 mL; CAMPHOR (NATURAL) 20 [hp_X]/1 mL; MATRICARIA CHAMOMILLA 20 [hp_X]/1 mL; BLACK COHOSH 20 [hp_X]/1 mL; CINCHONA OFFICINALIS BARK 20 [hp_X]/1 mL; ARABICA COFFEE BEAN 20 [hp_X]/1 mL; CYPRIPEDIUM PARVIFLORUM VAR. PUBESCENS ROOT 20 [hp_X]/1 mL; GELSEMIUM SEMPERVIRENS ROOT 20 [hp_X]/1 mL; HOPS 20 [hp_X]/1 mL; HYOSCYAMUS NIGER 20 [hp_X]/1 mL; STRYCHNOS IGNATII SEED 20 [hp_X]/1 mL; POTASSIUM BROMIDE 20 [hp_X]/1 mL; STRYCHNOS NUX-VOMICA SEED 20 [hp_X]/1 mL; PASSIFLORA INCARNATA FLOWERING TOP 20 [hp_X]/1 mL; ANEMONE PULSATILLA 20 [hp_X]/1 mL; SCUTELLARIA LATERIFLORA WHOLE 20 [hp_X]/1 mL; SEPIA OFFICINALIS JUICE 20 [hp_X]/1 mL; THUJA OCCIDENTALIS LEAFY TWIG 20 [hp_X]/1 mL; VALERIAN 11 [hp_X]/1 mL
INACTIVE INGREDIENTS: ALCOHOL; WATER

I-Sleep 4844L

INDICATIONS & USAGE SECTION

Formulated for symptoms associated with sleeplessness such as frequent waking, restlessness and the inability to fall asleep or return to sleep after waking.

DOSAGE & ADMINISTRATION SECTION

Directions: Ages 12 and up, take 6 drops by mouth (ages 0 to 11, give 3 drops) one hour before bedtime, and then again at bedtime. Repeat as needed or as directed by a health professional.

OTC - ACTIVE INGREDIENT SECTION

Equal parts of Passiflora incarnata 11x, Valeriana officinalis 11x, Absinthium 20x, Anacardium orientale 20x, Argentum nitricum 20x, Bryonia 20x, Calcarea carbonica 20x, Camphora 20x, Chamomilla 20x, Cimicifuga racemosa 20x, Cinchona officinalis 20x, Coffea cruda 20x, Cypripedium pubescen 20x, Gelsemium sempervirens 20x, Humulus lupulus 20x, Hyoscyamus niger 20x, Ignatia amara 20x, Kali bromatum 20x, Passiflora incarnata 20x, Pulsatilla 20x, Scutellaria lateriflora 20x, Sepia 20x, Thuja occidentalis 20x, Arsenicum album 20x, Belladonna 20x, Nux vomica 20x

OTC - PURPOSE SECTION

Formulated for symptoms associated with sleeplessness such as frequent waking, restlessness and the inability to fall asleep or return to sleep after waking.

INACTIVE INGREDIENT SECTION

Inactive Ingredients: USP Purified Water; USP Gluten-free, non-GMO, organic cane alcohol 20%.

QUESTIONS SECTION

newtonlabs.net – Questions? 800.448.7256

Newton Laboratories, Inc. FDA Est # 1051203 - Conyers, GA 30013

WARNINGS SECTION

WARNINGS: Keep out of reach of children. Do not use if tamper-evident seal is broken or missing. If symptoms worsen or persist for more than a few days, consult a doctor. If pregnant or breast-feeding, ask a doctor before use.

OTC - PREGNANCY OR BREAST FEEDING SECTION

If pregnant or breast-feeding, ask a doctor before use.

OTC - KEEP OUT OF REACH OF CHILDREN SECTION

Keep out of reach of children.